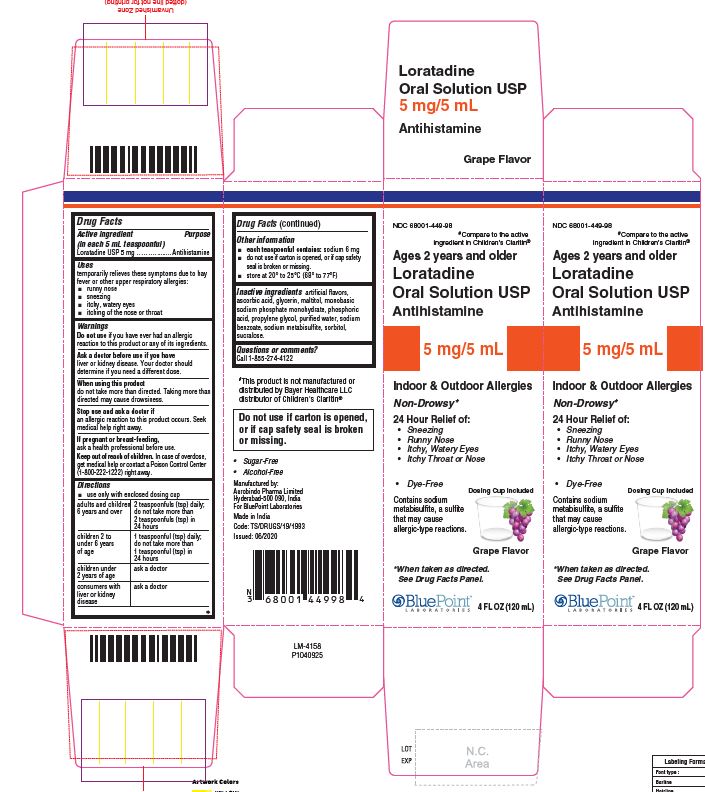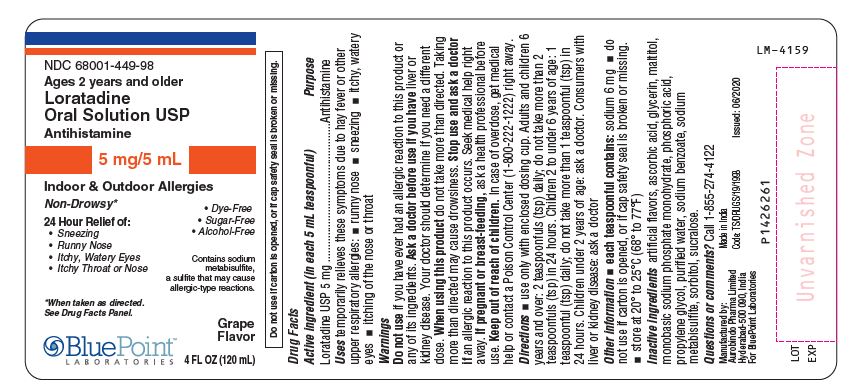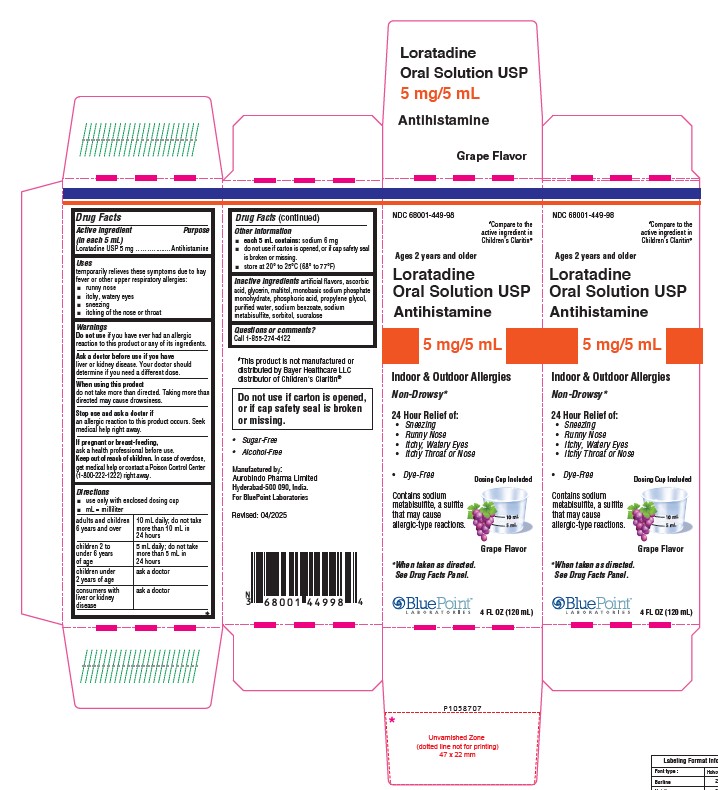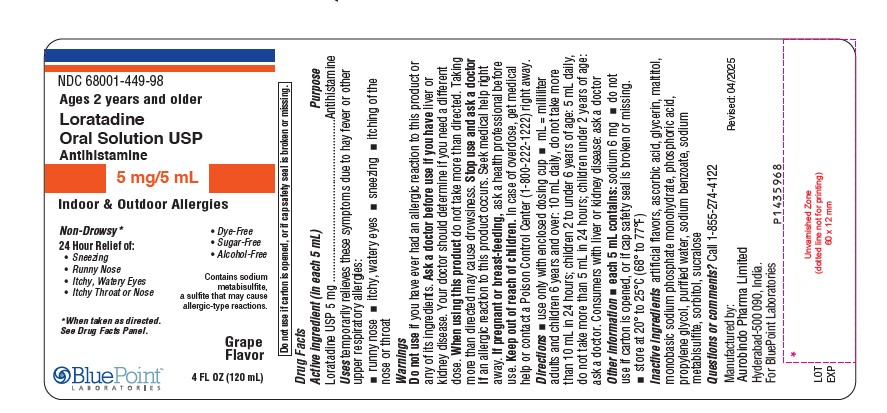 DRUG LABEL: Loratadine
NDC: 68001-449 | Form: SOLUTION
Manufacturer: BluePoint Laboratories
Category: otc | Type: HUMAN OTC DRUG LABEL
Date: 20250515

ACTIVE INGREDIENTS: LORATADINE 5 mg/5 mL
INACTIVE INGREDIENTS: GRAPE; ASCORBIC ACID; GLYCERIN; MALTITOL; SODIUM PHOSPHATE, MONOBASIC, MONOHYDRATE; PHOSPHORIC ACID; PROPYLENE GLYCOL; WATER; SODIUM BENZOATE; SODIUM METABISULFITE; SORBITOL; SUCRALOSE

Loratadine Oral Solution USP 5 mg/5 mL

Drug Facts

Active ingredient (in each 5 mL)
Loratadine USP 5 mg

Purpose

Antihistamine

Uses

temporarily relieves these symptoms due to hay fever or other upper respiratory allergies:

- runny nose
- itchy, watery eyes
- sneezing
- itching of the nose or throat

Warnings

Do not use if you have ever had an allergic reaction to this product or any of its ingredients.

Ask a doctor before use if you have

liver or kidney disease. Your doctor should determine if you need a different dose.

When using this product

do not take more than directed. Taking more than directed may cause drowsiness.

Stop use and ask a doctor if

an allergic reaction to this product occurs. Seek medical help right away.

If pregnant or breast-feeding,

ask a health professional before use.

Keep out of reach of children.

In case of overdose, get medical help or contact a Poison Control Center (1-800-222-1222) right away.

Directions

- use only with enclosed dosing cup
- mL= milliliter

adults and children 6 years and over | 10mL daily; do not take more than 10mL in 24 hours
children 2 to under 6 years of age | 5mL daily; do not take more than 5mL in 24 hours
children under 2 years of age | ask a doctor
consumers with liver or kidney disease | ask a doctor

Other information

- each 5mLcontains: sodium 6 mg
- do not use if carton is opened, or if cap safety seal is broken or missing.
- store at 20° to 25°C (68° to 77°F)

Inactive ingredients

artificial flavors, ascorbic acid, glycerin, maltitol, monobasic sodium phosphate monohydrate, phosphoric acid, propylene glycol, purified water, sodium benzoate, sodium metabisulfite, sorbitol, sucralose.

Questions or comments?

Call 1-855-274-4122
Manufactured by:
Aurobindo Pharma Limited
Hyderabad-500 090, India

For BluePoint Laboratories

Code:TS/DRUGS/19/1993

Revised: 04/2025

PACKAGE LABEL-PRINCIPAL DISPLAY PANEL - 5 mg/5 mL (120 mL Bottle)

NDC 68001-449-98
Ages
2 years
and older

Loratadine
Oral Solution USP
5 mg/5 mL
Antihistamine
Non-Drowsy*
24 Hour Relief of:

- Sneezing
- Runny Nose
- Itchy, Watery Eyes
- Itchy Throat or Nose

Do not use if carton is opened,
or if cap safety seal is broken
or missing.

- Dye-Free
- Sugar-Free
- Alcohol Free

Indoor & Outdoor Allergies

Contains sodium metabisulfite,
a sulfite that may cause
allergic-type reactions.

* When taken as directed. See Drug Facts Panel.
Grape Flavor
4FL OZ (120 mL)

PACKAGE LABEL-PRINCIPAL DISPLAY PANEL - 5 mg/5 mL Carton (120 mL)

NDC 68001-449-98

#Compare to the
active ingredient in
children’s Claritin®

Ages

2years
and older
Loratadine
Oral Solution USP
5 mg/5 mL
Antihistamine
Non-Drowsy*
24 Hour Relief of:

- Sneezing
- Runny Nose
- Itchy,watery Eyes
- Itchy Throat or Nose

Indoor & Outdoor Allergies
Dosing Cup Included

- Dye-Free
- Sugar-Free
- Alcohol Free

Contains sodium metabisulfite, a sulfite that may cause allergic-type reactions.

* When taken as directed.

See Drug Facts Panel.
Grape

Flavor
4 FL OZ (120 mL)